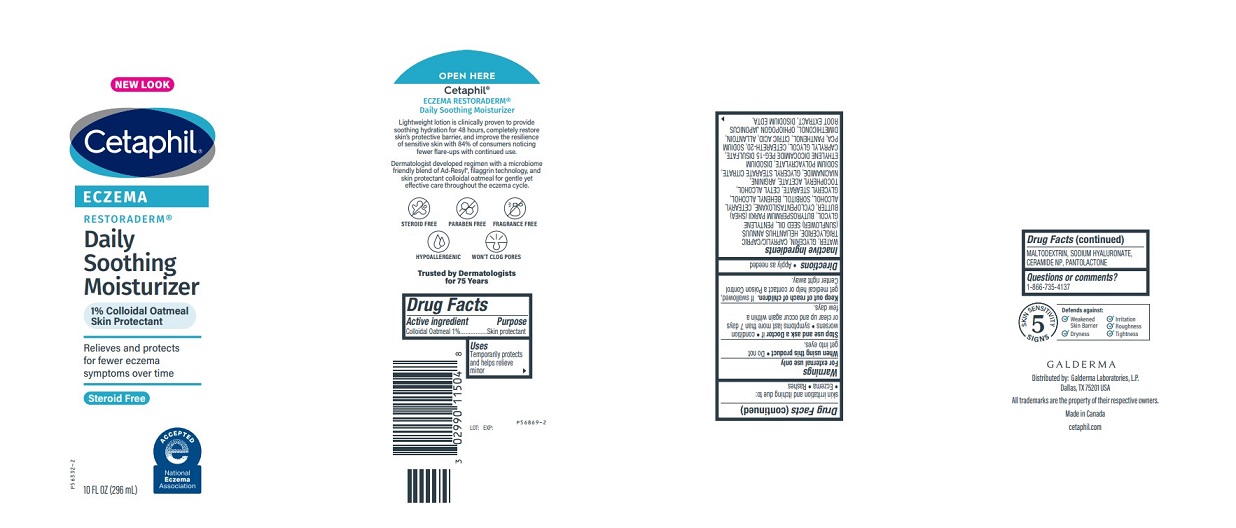 DRUG LABEL: Cetaphil Eczema Soothing Moisturizer
NDC: 0299-4128 | Form: LOTION
Manufacturer: Galderma Laboratories, L.P.
Category: otc | Type: HUMAN OTC DRUG LABEL
Date: 20240502

ACTIVE INGREDIENTS: Oatmeal 1 g/100 mL
INACTIVE INGREDIENTS: Water; Glycerin; Medium-Chain Triglycerides; Sunflower Oil; Pentylene Glycol; Sheanut Oil; Cyclomethicone 5; Cetostearyl Alcohol; Sorbitol; Docosanol; Glyceryl Monostearate; Cetyl Alcohol; .Alpha.-Tocopherol Acetate; Arginine; Niacinamide; Glyceryl Stearate Citrate; Sodium Polyacrylate (2500000 Mw); Disodium Ethylene Dicocamide Peg-15 Disulfate; Caprylyl Glycol; Polyoxyl 20 Cetostearyl Ether; Sodium Pyrrolidone Carboxylate; Panthenol; Citric Acid Monohydrate; Allantoin; Dimethiconol (100000 Cst); Ophiopogon Japonicus Root; Edetate Disodium; Maltodextrin; Hyaluronate Sodium; Ceramide Np; Pantolactone, (R)-

Drug Facts

Active ingredients......Purpose

Colloidal Oatmeal 1%......Skin Protectant

Uses

Temporarily protects and helps relieve minor skin irritation and itching due to:
●Eczema ●Rashes

Warnings

For external use only.

When using this product ● Do not get into eyes.

Stop use and ask a Doctor if ● condition worsens ● symptoms last more than 7 days or clear up and occur again within a few days.

Keep out of reach of children. If swallowed, get medical help or contact a Poison Control Center right away.

Directions

Apply as needed

Inactive Ingredients

WATER, GLYCERIN, CAPRYLIC/CAPRIC TRIGLYCERIDE, HELIANTHUS ANNUUS (SUNFLOWER) SEED OIL, PENTYLENE GLYCOL, BUTYROSPERMUM PARKII (SHEA) BUTTER, CYCLOPENTASILOXANE, CETEARYL ALCOHOL, SORBITOL, BEHENYL ALCOHOL, GLYCERYL STEARATE, CETYL ALCOHOL, TOCOPHERYL ACETATE, ARGININE, NIACINAMIDE, GLYCERYL STEARATE CITRATE, SODIUM POLYACRYLATE, DISODIUM ETHYLENE DICOCAMIDE PEG-15 DISULFATE, CAPRYLYL GLYCOL, CETEARETH-20, SODIUM PCA, PANTHENOL, CITRIC ACID, ALLANTOIN, DIMETHICONOL, OPHIOPOGON JAPONICUS ROOT EXTRACT, DISODIUM EDTA, MALTODEXTRIN, SODIUM HYALURONATE, CERAMIDE NP, PANTOLACTONE

Questions or comments?

1-866-735-4137

Distributed By:
Galderma Laboratories, L.P.
Dallas, TX 75201 USA

All trademarks are the property of their respective owners

Made in Canada

cetaphil.com

PRINCIPLE DISPLAY PANEL - 10 FL OZ bottle

NEW LOOK
Cetaphil®

ECZEMA

RESTORADERM®

Daily
Soothing
Moisturizer

1% Colloidal Oatmeal
Skin Protectant

Relieves and protects
for fewer eczema
symptoms over time

Steroid Free

National Eczema Association logo

10 FL OZ (296 mL)
P56332-2